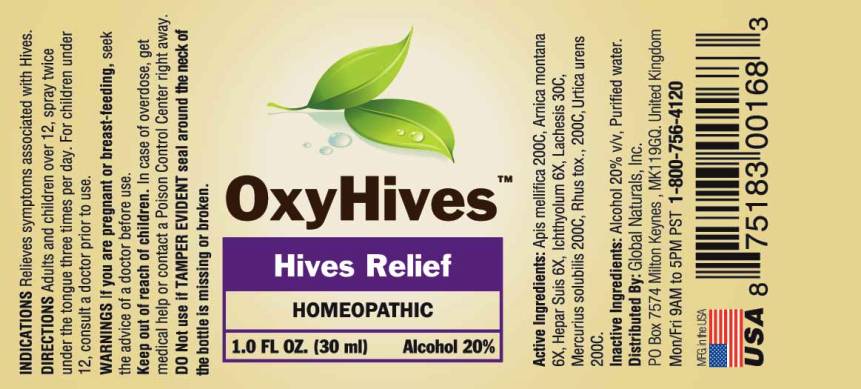 DRUG LABEL: Oxyhives
NDC: 43695-0010 | Form: SPRAY
Manufacturer: Global Naturals, Inc.
Category: homeopathic | Type: HUMAN OTC DRUG LABEL
Date: 20160504

ACTIVE INGREDIENTS: APIS MELLIFERA 200 [hp_C]/1 mL; ARNICA MONTANA 6 [hp_X]/1 mL; PORK LIVER 6 [hp_X]/1 mL; ICHTHAMMOL 6 [hp_X]/1 mL; LACHESIS MUTA VENOM 30 [hp_C]/1 mL; MERCURIUS SOLUBILIS 200 [hp_C]/1 mL; TOXICODENDRON PUBESCENS LEAF 200 [hp_C]/1 mL; URTICA URENS 200 [hp_C]/1 mL
INACTIVE INGREDIENTS: WATER; ALCOHOL

DRUG FACTS:

ACTIVE INGREDIENTS:

Apis Mellifica 200C, Arnica Montana 6X, Hepar Suis 6X, Ichthyolum 6X, Lachesis Mutus 30C, Mercurius Solubilis 200C, Rhus Tox 200C, Urtica Urens 200C.

INDICATIONS:

Relieves symptoms associated with Hives.

WARNINGS:

If you are pregnant or breast-feeding, seek the advice of a doctor before use.

Keep out of reach of children. In case of overdose, get medical help or contact a Poison Control Center right away.

DO Not use if TAMPER EVIDENT seal around the neck of the bottle is missing or broken.

Keep out of reach of children. In case of overdose, get medical help or contact a Poison Control Center right away.

DIRECTIONS:

Adults and children over 12, spray twice under the tongue three times per day.

For children under 12, consult a doctor prior to use.

INDICATIONS:

Relieves symptoms associated with Hives.

INACTIVE INGREDIENTS:

Alcohol 20% v/v, Purified water.

QUESTIONS:

Distributed By: Global Naturals, Inc.

PO Box 7574 Milton Keynes, MK119GQ, United Kingdom

Mon/Fri 9AM to 5PM PST 1-800-756-4120

PACKAGE LABEL DISPLAY:

OxyHives

Hives Relief

HOMEOPATHIC

1.0 FL OZ. (30 ml)